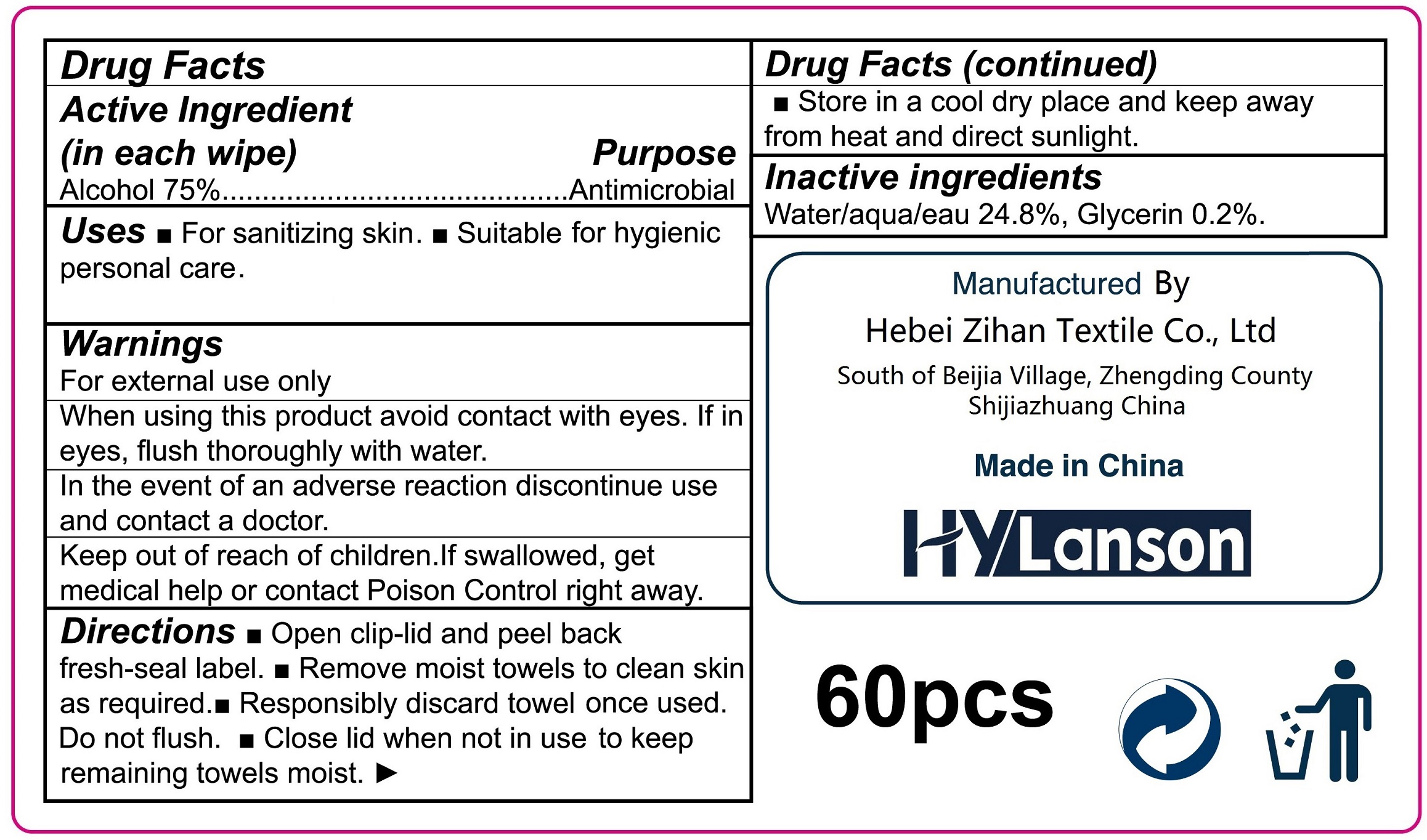 DRUG LABEL: HyLanson Alcohol Wipes 5.9inX7.9in
NDC: 77678-004 | Form: CLOTH
Manufacturer: Hebei Zihan Textile Co., Ltd
Category: otc | Type: HUMAN OTC DRUG LABEL
Date: 20241219

ACTIVE INGREDIENTS: ALCOHOL 0.75 mL/1 mL
INACTIVE INGREDIENTS: WATER; GLYCERIN

HyLanson Alcohol Wipes 5.9inx7.9in

Active Ingredient (in each wipe)

Alcohol 75%

Purpose

Antimicrobial

Uses

- For sanitizing skin.
- Suitable for hygienic personal care.

Warnings

For external use only.

When using this product

avoid contact with eyes. If in eyes, flush thoroughly with water.

In the event of an adverse reaction discontinue use and contact a doctor.

Keep out of reach of children.

If swallowed, get medical help or contact a Poison Control Center right away.

Directions

- Open clip-lid and peel back fresh-seal label.
- Remove moist towels to clean skin as required.
- Responsibly discard towel once used. Do not flush.
- Close lid when not in use to keep remaining towels moist.
- Store in a cool dry place and keep away from heat and direct sunlight.

Inactive Ingredients

Water/aqua 24.8%, Glycerin 0.2%.